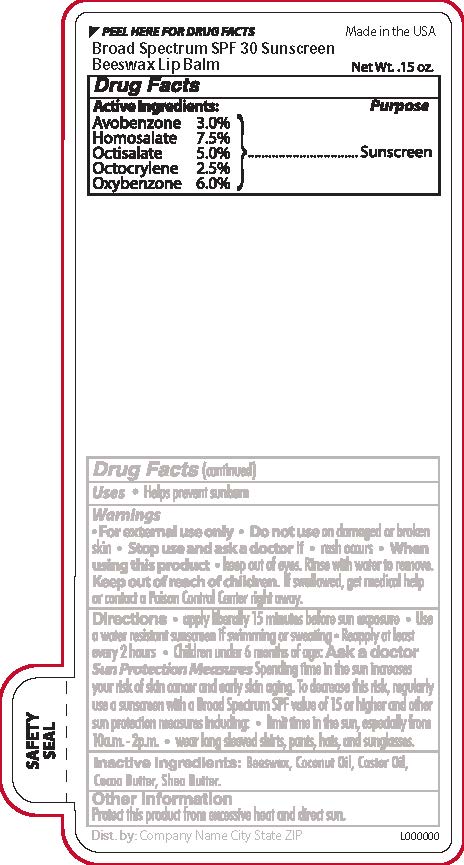 DRUG LABEL: Beeswax SPF 30 Broad Spectrum Lip Balm
NDC: 65692-0543 | Form: STICK
Manufacturer: Raining Rose, Inc
Category: otc | Type: HUMAN OTC DRUG LABEL
Date: 20231026

ACTIVE INGREDIENTS: AVOBENZONE 0.13 g/4.25 g; HOMOSALATE 0.32 g/4.25 g; OCTISALATE 0.21 g/4.25 g; OCTOCRYLENE 0.11 g/4.25 g; OXYBENZONE 0.26 g/4.25 g
INACTIVE INGREDIENTS: COCOA BUTTER; SHEA BUTTER; WHITE WAX; COCONUT OIL; CASTOR OIL

Active Ingredients

Avobenzone 2.0%

Octinoxate 6.5%

Octisalate 5.0%

Octocrylene 1.5%

Purpose

Sunscreen

Warnings

For external use only

Do not use

on damaged or broken skin.

Stop Use and ask a doctor if

Rash Occurs

When Using this Product

Keep out of eyes. Rinse well with water to remove.

Keep out of reach of children

If swallowed, get medical help or contact a Poison Control Center right away.

Directions

Apply liberally 15 minutes before sun exposure

Use a water resistant sunscreen if swimming or sweating

Reapply at least every 2 hours
Children under 6 months of age: Ask a doctor

Inactive ingredients:

Beeswax, coconut oil, castor oil, cocoa butter, shea butter.

DOSAGE AND ADMINISTRATION

Apply liberally 15 minutes before sun exposure

INDICATIONS AND USAGE

Helps prevent sunburn